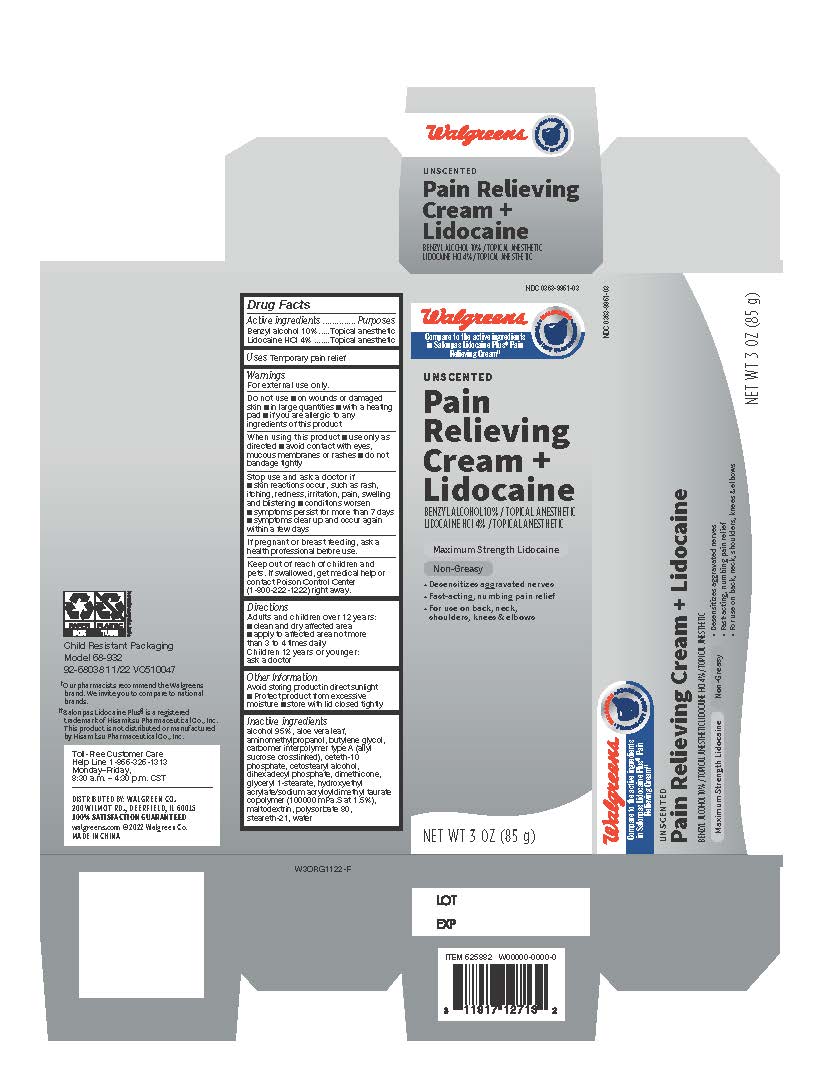 DRUG LABEL: Walgreens Lidocaine Plus Cream
NDC: 0363-9951 | Form: CREAM
Manufacturer: Walgreens Company
Category: otc | Type: HUMAN OTC DRUG LABEL
Date: 20240509

ACTIVE INGREDIENTS: BENZYL ALCOHOL 100 mg/1 g; LIDOCAINE HYDROCHLORIDE 40 mg/1 g
INACTIVE INGREDIENTS: DIMETHICONE; AMINOMETHYLPROPANOL; BUTYLENE GLYCOL; DIHEXADECYL PHOSPHATE; GLYCERYL 1-STEARATE; MALTODEXTRIN; CETOSTEARYL ALCOHOL; CETETH-10 PHOSPHATE; HYDROXYETHYL ACRYLATE/SODIUM ACRYLOYLDIMETHYL TAURATE COPOLYMER (45000 MPA.S AT 1%); POLYSORBATE 80; STEARETH-21; DEHYDRATED ALCOHOL; WATER; CARBOMER INTERPOLYMER TYPE A (55000 CPS); ALOE VERA LEAF

Unscented Pain Relieving Cream + Lidocaine

Active Ingredient

Benzyl alcohol 10%
Lidocaine HCl 4%

Purpose

Topical anesthetic

Uses

For temporary relief of pain

Warnings

For external use only

Do not Use

- on wounds or damaged skin
- in large quantities
- with a heating pad
- if you are allergic to any ingredients of this product

When using this product

- use only as directed
- avoid contact with the eyes, mucous membranes or rashes
- do not bandage tightly

Stop use and ask a doctor

- skin reactions occur, such as rash, itching, redness, irritation, pain, swelling, and blistering
- conditions worsen
- symptoms persist for more than 7 days
- symptoms clear up and occur again within a few days

If pregnant or breast-feeding

ask a health professional before use.

Keep out of reach of children

If swallowed, get medical help or contact a Poison Control Center (1-800-222-1222) right away.

Directions

Adults and children over 12 years :

- clean and dry affected area
- apply to affected area not more than 3 to 4 times daily

Children under 12 years of age:
consult a doctor

Other Information

- Avoid storing product in direct sunlight
- Protect product from excessive moisture
- Store with lid closed tighly

Inactive Ingredients

alcohol 95%, aloe vera leaf, aminomethylpropanol, butylene glycol,carbomer interpolymer type A (allylsucrose crosslinked), ceteth-10
phosphate, cetostearyl alcohol, dihexadecyl phosphate, dimethicone,glyceryl 1-stearate, hydroxyethyl acrylate/sodium acryloyldimethyl taurate copolymer (1001.5%), maltodextrin, polysorbate 80, steareth-21, water

Questions or comments?

Toll-Free Customer Care
Help Line 1-866-326-1313
Monday–Friday,
8:30 a.m. – 4:30 p.m. CST